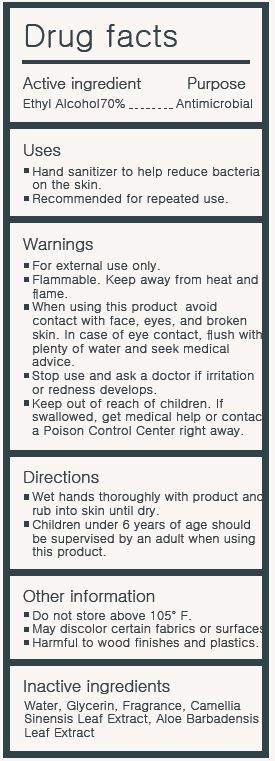 DRUG LABEL: ManiMe MOISTURIZING HAND SANITIZER
NDC: 74122-0013 | Form: LIQUID
Manufacturer: CH Harmony Co., Ltd.
Category: otc | Type: HUMAN OTC DRUG LABEL
Date: 20200507

ACTIVE INGREDIENTS: ALCOHOL 42 mL/60 mL
INACTIVE INGREDIENTS: WATER; GREEN TEA LEAF; ALOE VERA LEAF; GLYCERIN

CH Harmony Co., Ltd. - ManiMe MOISTURIZING HAND SANITIZER

ACTIVE INGREDIENT

Alcohol

INACTIVE INGREDIENT

water, glycerin, camellia sinensis leaf extract, aloe barbadensis leaf extract, frgrance

PURPOSE

Antiseptic

keep out of reach of the children

INDICATIONS AND USAGE

Wet hands thoroughly with product and rub into skin until dry.

Children under 6 years of age should be supervised by an adult when using this product.

WARNINGS

For external use only.

Flammable.

Keep away from fire or flame.

DOSAGE AND ADMINISTRATION

for external use only